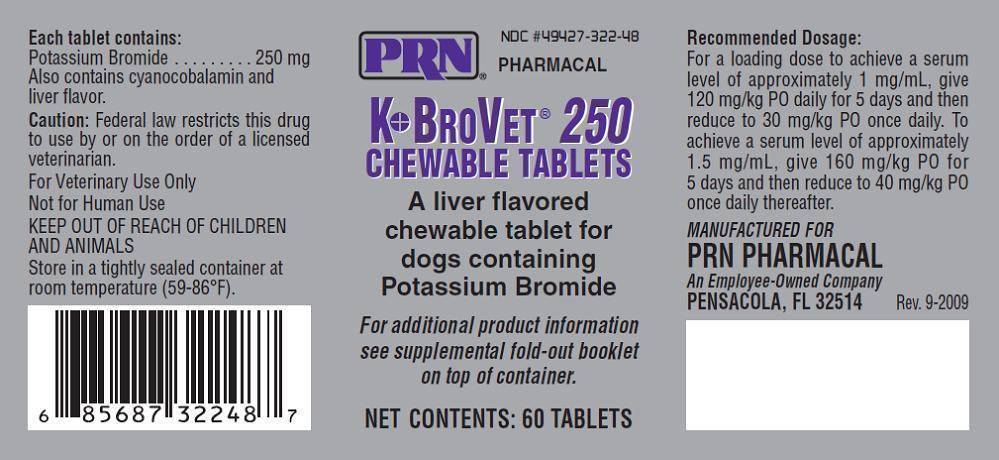 DRUG LABEL: K-BroVet 250
NDC: 49427-322 | Form: TABLET, CHEWABLE
Manufacturer: Pegasus Laboratories, Inc.
Category: animal | Type: PRESCRIPTION ANIMAL DRUG LABEL
Date: 20241213

ACTIVE INGREDIENTS: POTASSIUM BROMIDE 250 mg/1 1
INACTIVE INGREDIENTS: MICROCRYSTALLINE CELLULOSE 192.9 mg/1 1; DIBASIC CALCIUM PHOSPHATE DIHYDRATE 133 mg/1 1; CYANOCOBALAMIN 6.5 mg/1 1; STEARIC ACID 60.5 mg/1 1

Caution:

Federal law restricts this drug to use by or on the order of a licensed veterinarian. Contains a new animal drug for use only in investigational animals in clinical trials. Not for use in humans. Edible products of investigational animals are not to be used for food unless authorization has been granted by the U.S. Food and Drug Administration or by the U.S. Department of Agriculture.

Rev. 10-2015

Product Information

See WARNINGS concerning use in animals with certain conditions.

DESCRIPTION

K●BroVET® Chewable Tablets are liver flavored tablets containing 250 mg or 500 mg of potassium bromide and cyanocobalamin.

Indications:

Anticonvulsant

How Supplied:

250mg Tablet (60ct) bottle

NDC 49427-322-48

Storage Conditions:

Store in a tightly sealed container at room temperature (59-86F).

Keep out of reach of children and animals.

INDICATION

K●BroVET® potassium bromide is used to treat seizure disorders in dogs. It can be used in addition to therapy with other agents or as the sole anticonvulsant.

CONTRAINDICATIONS

K●BroVET® should not be used in animals with a history of hypersensitivity to Bromide or any of the com-ponents of the solution or tablets.

DOSAGE AND ADMINISTRATION

Recommended Dosage for K●BroVET® Oral Solution and Tablets:

To achieve a serum level of approximately 1 mg/mL, give 120 mg/kg PO daily for 5 days then reduce to 30mg/kg PO once daily. To achieve a serum level of approximately 1.5 mg/mL, give 160 mg/kg PO for 5 days and then reduce to 40 mg/kg PO once daily thereafter.{R-21}

Among dogs responses to bromide may vary, treatment should be tailored to the individual dog, based on serum bromide concentration, success of seizure control, and the observation of adverse effects. Steady state serum concentrations generally take 4 to 5 months in dogs; therapeutic concen-trations may be reached before steady state at about 4 weeks after the beginning of treatment, serum bromide concentration may be tested to assess the response to product and, if results are satisfactory, the next testing for steady state serum levels is typically about 4 months. If the dog’s serum concentration is within range and the dog is doing well in the therapeutic range, serum concentration may then be tested every 6 to 12 months. Serum bromide is typically evaluated at the end of the loading period, then as described above when an animal is started with a loading dose.

Dogs― An oral dose of 30 mg of Bromide per kg of body weight every twelve hours for 115 days produced a steady state serum concen- tration of 2.45 mg/mL (range, 1.78 to 2.69 mg/mL) in Beagles fed a diet contain-ing 0.55% chloride.{R-3}

WARNINGS

This medication should be used cautiously in older animals as they will be more susceptible to adverse effects. This medication is not indicated for use in cats.

Possible Side Effects:

Dog may experience drowsi-ness when taking , but this will generally go away after approximately 3 weeks. Increased hunger, thirst, urination, vomiting, constipation, anorexia, and uncoordinated movements may occur with . During the load in dose increased nausea may be experienced.

There is no information on the relative frequency of pan-creatitis in dogs associated with bromide therapy alone. However, pancreatitis has been reported to be more frequent in dogs on concurrent phenobarbital and bro-mide therapy than dogs on phenobarbital alone.{R-12}

Personality changes have been occasionally reported in dogs on bromide, including attention seeking, irritability or aggression, and aimless pacing.

Reproduction/Pregnancy/Lactation

The effects of bromide on canine reproduction have not been studied.

Young Dogs

Safety of administering bro-mide to neonates and young animals has not been evaluated.{R-16-17}

Drug interactions and/or related effects have been selected on the basis of their clinical significance (possible mechanism in parentheses where appropriate) ― not necessar-ily inclusive (»=major clinical significance):

Note: Any of the following medications taken in combinations, depending on the amount taken, could also interact with K●BroVET®

Medications and foods containing chloride, bromide and chloride compete for reabsorption by the kidneys; increased amounts of chloride can promote loss of bromide in the urine, leading to a lowering of serum bromide concentrations: Decreased chloride consumption will promote increased renal reabsorption of bromide.{R-1; 2; 4; 5; 7; 15}

Halothane anesthesia (when inhaled a percentage of halothane is metabolized by dogs to produce bromide, along with other compounds; peak serum concentration occurs within about a day and, in one group of dogs, ranged from 0.04 to 0.088 mg/mL and persisted, with some diminishment, for at least ten days.{R-10; 11} Consideration should be given to animals that must have repeated anesthesia or that already require high serum bromide concentration for seizure control. Increased bromide levels due to metabolism of halothane are unlikely to be a significant risk for bromide toxicity in most dogs.

Mechanism of action/Effect:

Bromide's mechanism of action has not been clearly defined. By preferential movement across neuronal membranes via gamma-aminio butyric (GABA) - activated chloride channels, bromide may aid in controlling seizures through hyperpolarization of neuronal cell membranes, leading to stabilization and decreased sensitivity to epileptic foci. {R-2; 15}

Volume of distribution

Dogs: 0.45 ± 0.07 L/kg{R-4}

Protein binding: Bromide is minimally protein bound.{R-20}

Biotransformation: Bromide is not biotransformed by the liver and is eliminated unchanged, primarily by renal clearance.{R-2}

Half-life: Elimination ―

Bromide is freely filtered by the glomerulus, but is reabsorbed by the kidneys, in competition with chloride.{R-7}

Bromide reabsorption will predominate in the absence of a large chloride load, causing a significantly extended elimination half-life in dogs.{R-4; 5; 7} Increasing chloride intake by an animal on a low chloride diet will decrease the half-life of elimination.{R-14; 15}

Elimination: Renal. Because bromide is widely distrib-uted, minute amounts will also be excreted in saliva, sweat and feces.{R-5; 6} Rate of elimination of bromide will increase in dogs that receive a high level of chlo-ride supplementation.{R-4}

OVERDOSE

For more information in cases of overdose or unintentional ingestion, contact the American Society for the Prevention of Cruelty to Animals (ASPCA) National Animal Poison Control Center (888-426-4435 or 900-443-0000; a fee may be required for consultation) and/or the drug manufacturer.

Note: Signs of bromide toxicity are dose-related but dogs differ in their sensitivity. Bromide toxicity has rarely been reported in dogs with serum bromide concentrations of less than 1.5 mg/mL. Signs have been reported in some dogs with relatively low serum concen-tration (2.75 mg/mL) while not appearing in other dogs with significantly higher concen-tration (4 mg/mL).{R-3; 18} Dogs on concurrent bromide and phenobarbital therapy may be prone to bromide toxicity at lower serum concentrations than when bromide is administered alone. Other physical factors may also play a role in sensitivity.{R-3}

Short-term bromide toxicity is considered completely reversible.{R-18} However, mild bromide toxicity can progress to more severe nervous sys-tem dysfunction with ongoing high serum concentration of bromide.{R-8}

Other species ― Bromide toxicity has also been reported in cattle, goats and horses fed hay that contained bromide ion residue from accidental treatment with methyl bromide. Signs included ataxia, hind limb weakness, joint swelling, and sedation or recumbency.{R-9}

Clinical effects of overdose

Clinical signs may appear with serum bromide concen-tration >1.5 mg/mL in dogs on bromide therapy alone, but become more common as serum concentration increases, and most com-mon when serum concen-tration exceeds 4 mg/mL in dogs receiving bromide as the only anticonvulsant (2 to 3 mg/mL in dogs receiving concurrent phenobarbital and bromide).{R-3; 18}

Ataxia; diarrhea; hematochezia; salivation, excessive; shivering; skin lesions; stupor, progressing to coma and death – Reported with a dose of 200 to 500 mg/kg a day for 4 to 26 weeks.{R-13}

Treatment of bromide toxicity

Recommended treatment consists of the following:

For dogs on concurrent phenobarbital and bromide therapy with mild sedation, ataxia or hind limb weak-ness, a 10 to 25% reduction in phenobarbital may resolve the signs within five to seven days.{R-19}

For dogs receiving bromide as the only anticonvulsant, K●BroVET® may be discontinued for a few days while monitoring serum concentration, to see if mild signs of toxicity will resolve.

If necessary, renal excretion of bromide may be accelerated by increasing sodium chloride consumption or administering 0.9% sodium chloride intravenously over twelve hours, depending on the severity of the toxicity.R-7; 8; 13}

Supportive treatment

Continue to monitor

References

1. Podell M, Fenner WR. Bromide therapy in refractory canine idiopathic epilepsy. J Vet Intern Med (1993) Sep-Oct. 7(5):318-27.

2. Trepanier, L.A. Use of bromide as an anticonvulsant for dogs with epilepsy. J Am Vet Med Assoc. 1995 Jul 15, 207(2) 163-6.

3. March PA, Podell M, Sams RA.Pharmacokinetics and toxicity of bromide following high-dose oral potassium bromide administration in healthy beagles. J Vet Pharmacol Ther 2002, 25:425-32.

4. Trepanier LA, Babish JG. Pharmacokinetic properties of bromide in dogs after intravenous and oral administration of single doses. Res Vet Sci 1995, 58 248-51.

5. Wolf RL., Eadie GS. Reabsorption of bromide by the kidney. AM S Physiol 1950. 163(2) 436-41.

6. USP Committee comment. Rec 9/9/04.

7. Palmer JW, Clarke HT. The elimination of bromides from the blood stream. J Biol Chem 1933; 99:435.

8. Yohn SE, Morrison WB, Sharp PE. Bromide toxicosis (bromism) in a dog treated with potassium bromide for refractory seizures. J AM Vet Med Assoc 1992 Aug 1, 201(13) 468-70.

9. Knight HD, Costner GC. Bromide intoxication of horses, goats and cattle. J Am Vet Med Assoc 1977 Sept 1; 171(5):446-8.

10. Pedersoli WM. Serum bromide concentrations during and after halothane anesthesia in dogs. Am J Vet Res 1980 Jan; 41(1) 77-80.

11. De Moor A, Van Den Hende C, Moens Y et al. Increased plasma bromide concentrations in the horse after halothane anesthesia. Am J Vet Res 1978 Oct. 39(10): 1624-6.

12. Gaskill CL, Cribb AE. Pancreatitis associated with potassium bromide/phenobarbital combination therapy in epileptic dogs. Can Vet L 2000 Jul, 4: 555-8.

13. Nichols ES, Trepanier LA, Linn K. Bromide toxicosis secondary to renal insufficiency in an epileptic dog. J Am Vet Med Assoc 1996 Jan 15, 208(2) 231-3.

14. Shaw N, Trepanier LA, Garland S. High dietary chloride content associated with loss of therapeutic serum bromide concentrations in an epileptic dog. J Am Vet Med Assoc 1996 Jan15.208 (2) 234-6.

15. Trepanier LA, Babish JG, Effect of dietary chloride content on the elimination of bromide by dogs. res vet Sci 1995; 58: 252-5.

16. Okuda K, Yasuhhara A, Kamei A, et al. Successful control with bromide of two patients with malignant migrating partial seizures in infancy. Brain Dev 2000 Jan; 22(1): 56-9

17. Ernst JP, Doose H, Baier WK. Bromides were effective in intractable epilepsy with generalized tonic-clonic seizures and onset in early childhood. Brain Dev 1988;10(6) 385-8.

18. Sisson A. Current experiences with anticonvulsants in dogs and cats. In: Proceedings of the fifteenth annual veterinary medical forum. Lakewood, Colorado: American College of Veterinary Internal Medicine 1997. p. 596-8.

19. Trepanier LA. Optimal bromide therapy and monitoring. In:Proceedings of the fifteenth annual veterinary medical forum. Lakewood, Colorado: American College of Veterinary Internal Medicine 1997. p. 100-101.

20. USP Committee comment, Rec 11/01/04.

21 Plumbs veterinary Handbook 6th Edition.